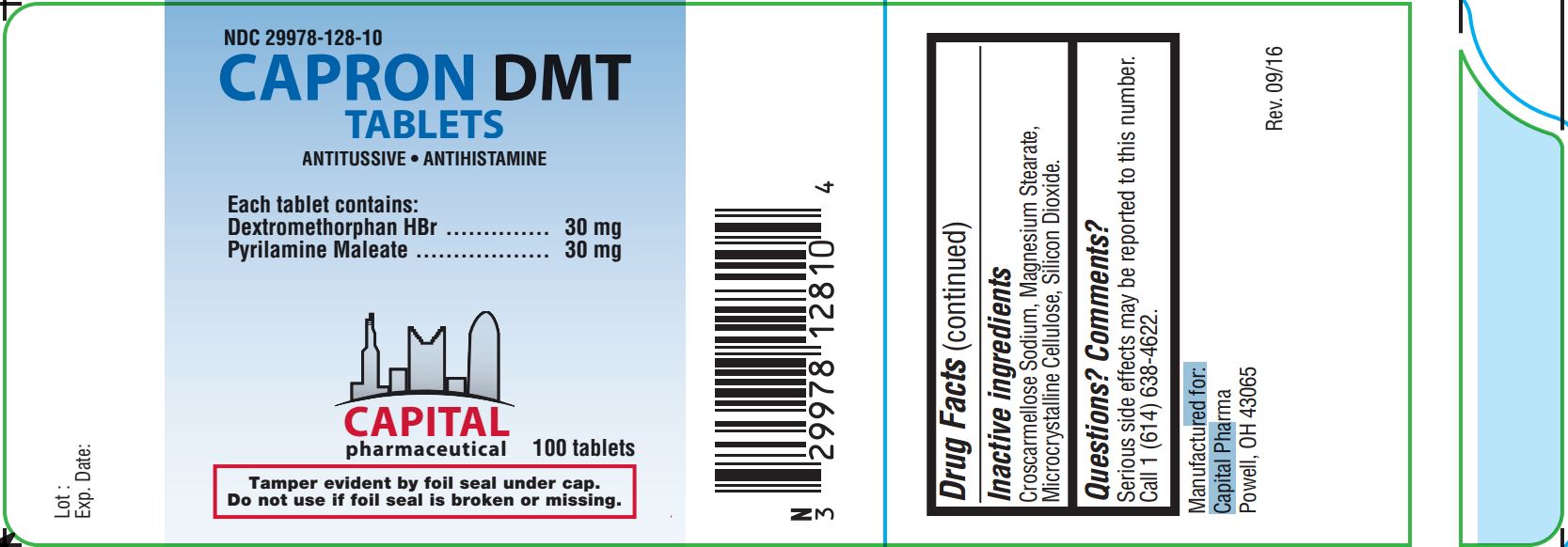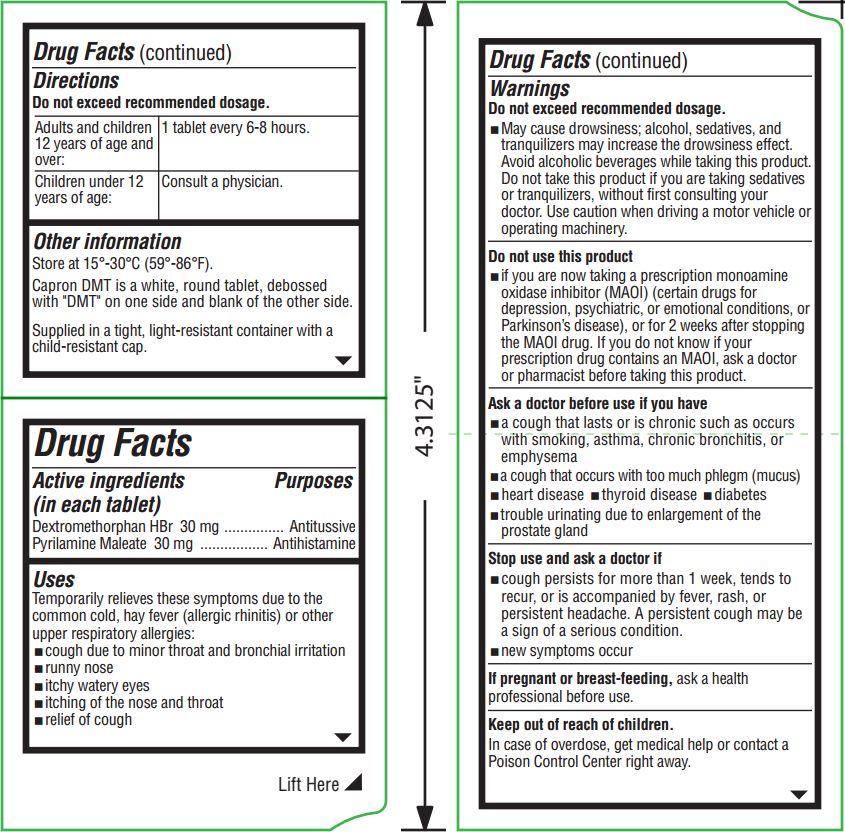 DRUG LABEL: Capron DMT
NDC: 29978-128 | Form: TABLET
Manufacturer: Capital Pharma
Category: otc | Type: HUMAN OTC DRUG LABEL
Date: 20251210

ACTIVE INGREDIENTS: DEXTROMETHORPHAN HYDROBROMIDE 30 mg/1 1; PYRILAMINE MALEATE 30 mg/1 1
INACTIVE INGREDIENTS: CROSCARMELLOSE SODIUM; MAGNESIUM STEARATE; SILICON DIOXIDE; MICROCRYSTALLINE CELLULOSE

Capron DMT Tablets

Directions

Do not exceed recommended dosage.

Adults and children 12 years of age and over: | 1 tablet every 6-8 hours.
Children under 12 years of age: | Consult a physician.

Other information

Store at 15o-30oC (59o-86oF).

Capron DMT is a white, round tablet, debossed with "DMT" on one side and blank of the other side.

Supplied in a tight, light-resistant container with a child-resistant cap.

Active ingredients (in each tablet)

Dextromethorphan HBr 30 mg

Pyrilamine Maleate 30 mg

Purposes

Antitussive

Antihistamine

Uses

Temporarily relieves these symptoms due to the common cold, hay fever (allergic rhinitis) or other upper respiratory allergies:

- cough due to minor throat and bronchial irritation
- runny nose
- itchy watery eyes
- itching of the nose and throat
- relief of cough

Do not exceed recommended dosage.

- May cause drowsiness; alcohol, sedatives, and tranquilizers may increase the drowsiness effect. Avoid alcoholic beverages while taking this product. Do not take this product if you are taking sedatives or tranquilizers, without first consulting your doctor. Use caution when driving a motor vehicle or operating machinery.

Do not use this product

- if you are now taking a prescription monoamine oxidase inhibitor (MAOI) (certain drugs for depression, psychiatric, or emotional conditions, or Parkinson's disease), or for 2 weeks after stopping the MAOI drug. If you do not know if your prescription contains an MAOI, ask a doctor or pharmacist before taking this product.

Ask a doctor before use if you have

- a cough that lasts or is chronic such as occurs with smoking, asthma, chronic bronchitis, or emphysema
- a cough that occurs with too much phlegm (mucus)
- heart disease
- thyroid disease
- diabetes
- trouble urinating due to enlargement of the prostate gland

Stop use and ask doctor if

- cough persists for more than 1 week, tends to recur, or is accompanied by fever, rash, or persistent headache. A persistent cough may be a sign of a serious condition.
- new symptoms occur

If pregnant or breast-feeding,

ask a health professional before use.

Keep out of reach of children.

In case of overdose, get medical help or contact a Poison Control Center right away.

Inactive ingredients

Croscarmellose Sodium, Magnesium Stearate,

Microcrystalline Cellulose, Silicon Dioxide.

Questions? Comments?

Serious side effects may be reported to this number.

Call 1 (614) 638-4622.

PACKAGE LABEL

Manufactured for:

Capital Pharma

Powell, OH 43065

Rev. 09/16